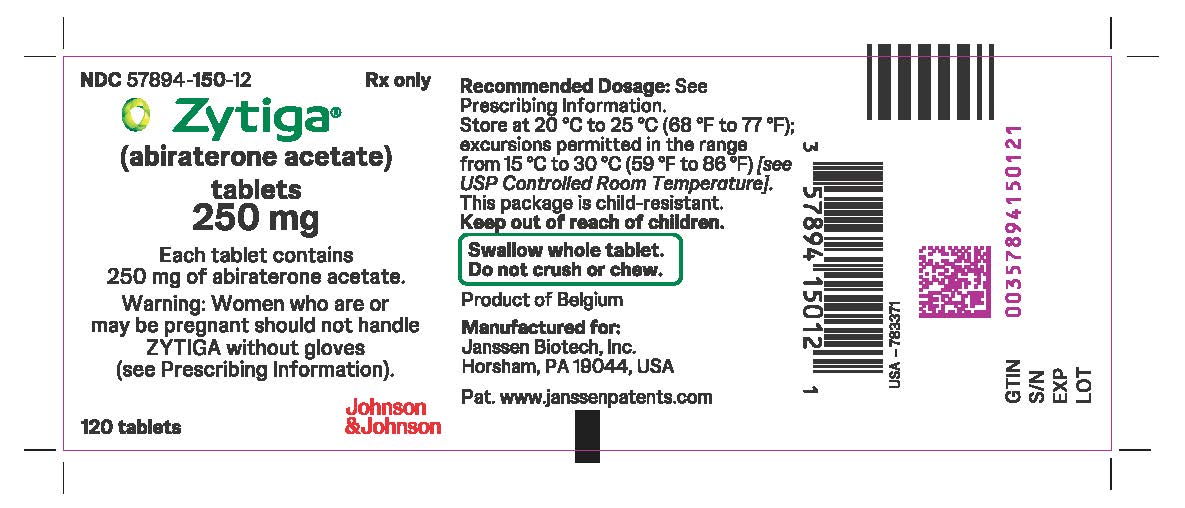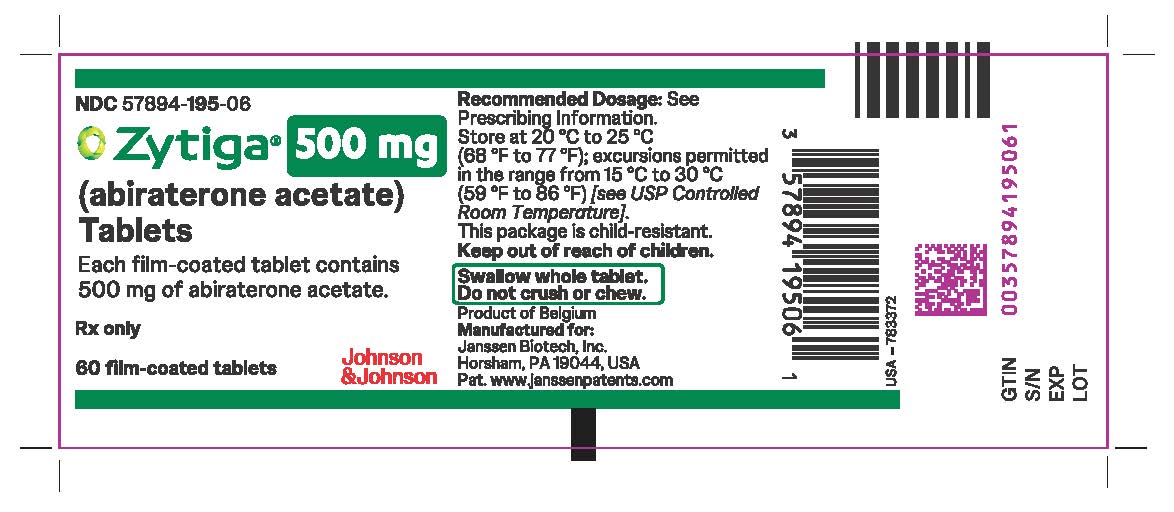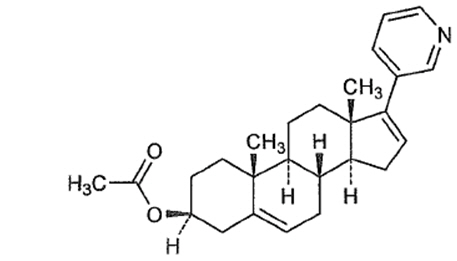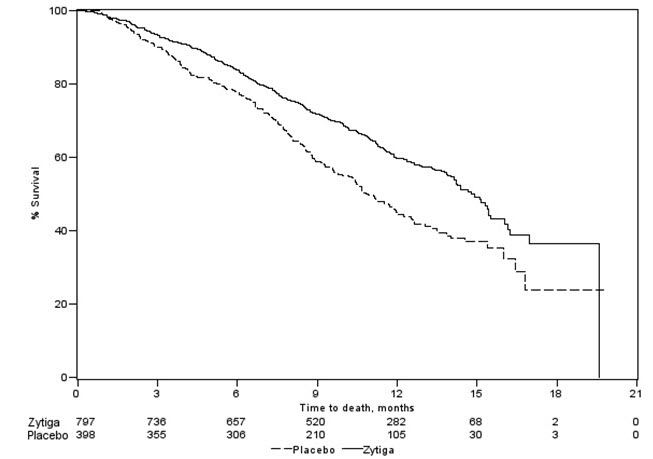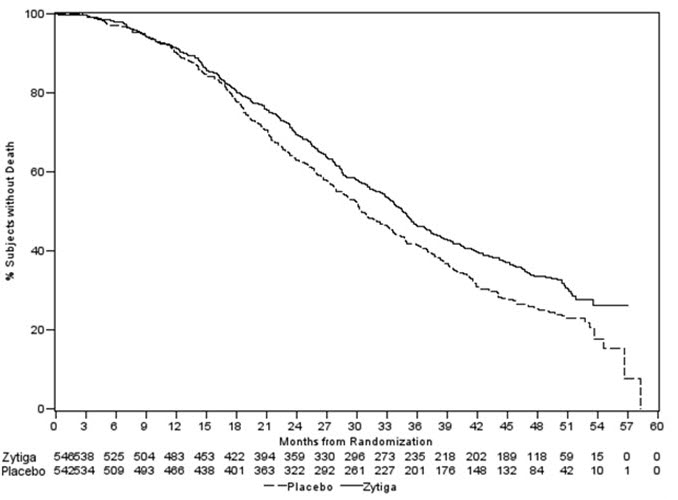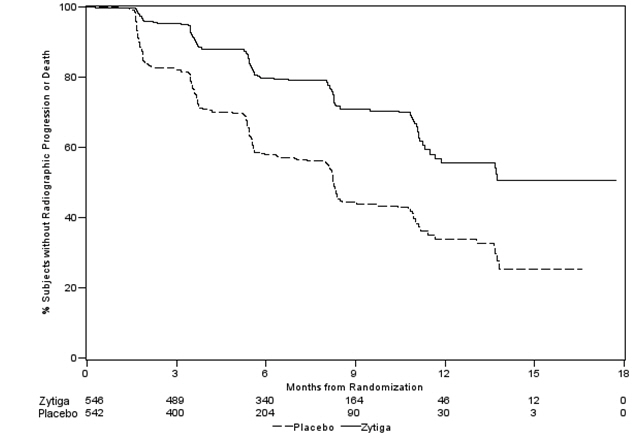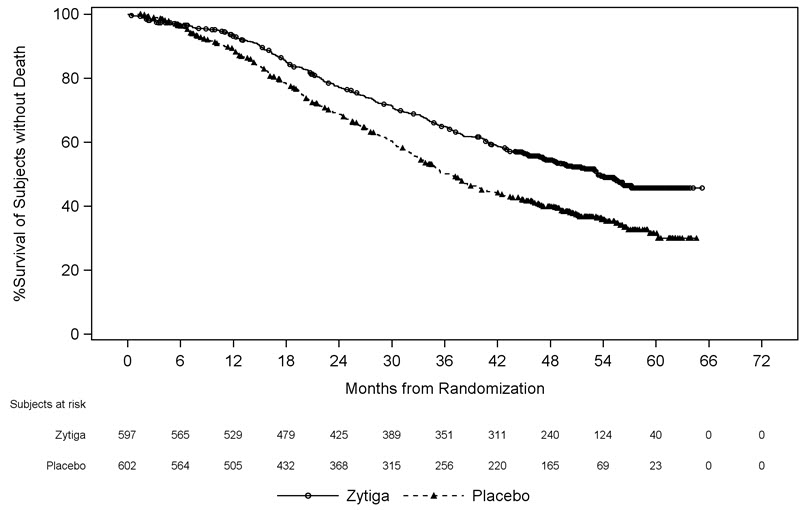 DRUG LABEL: Zytiga
NDC: 57894-150 | Form: TABLET
Manufacturer: Janssen Biotech, Inc.
Category: prescription | Type: HUMAN PRESCRIPTION DRUG LABEL
Date: 20250328

ACTIVE INGREDIENTS: ABIRATERONE ACETATE 250 mg/1 1
INACTIVE INGREDIENTS: LACTOSE MONOHYDRATE; MICROCRYSTALLINE CELLULOSE; CROSCARMELLOSE SODIUM; POVIDONE, UNSPECIFIED; SODIUM LAURYL SULFATE; MAGNESIUM STEARATE; SILICON DIOXIDE

HIGHLIGHTS OF PRESCRIBING INFORMATION

These highlights do not include all the information needed to use ZYTIGA safely and effectively. See full prescribing information for ZYTIGA.
ZYTIGA®(abiraterone acetate) tablets, for oral use
Initial U.S. Approval: 2011

1 INDICATIONS AND USAGE

ZYTIGA is a CYP17 inhibitor indicated in combination with prednisone for the treatment of patients with

- metastatic castration-resistant prostate cancer (CRPC). (1)
- metastatic high-risk castration-sensitive prostate cancer (CSPC). (1)

2 DOSAGE AND ADMINISTRATION

Metastatic castration-resistant prostate cancer:

- ZYTIGA 1,000 mg orally once daily with prednisone 5 mg orally twicedaily. (2.1)

Metastatic castration-sensitive prostate cancer:

- ZYTIGA 1,000 mg orally once daily with prednisone 5 mg orally oncedaily. (2.2)

Patients receiving ZYTIGA should also receive a gonadotropin-releasing hormone (GnRH) analog concurrently or should have had bilateral orchiectomy. ZYTIGA tablets must be taken as a single dose once daily on an empty stomach. Do not eat food 2 hours before and 1 hour after taking ZYTIGA. The tablets must be swallowed whole with water. Do not crush or chew tablets. (2.3)

Dose Modification:

- For patients with baseline moderate hepatic impairment (Child-Pugh Class B), reduce the ZYTIGA starting dose to 250 mg once daily. (2.4)
- For patients who develop hepatotoxicity during treatment, hold ZYTIGA until recovery. Retreatment may be initiated at a reduced dose. ZYTIGA should be discontinued if patients develop severe hepatotoxicity. (2.4)

3 DOSAGE FORMS AND STRENGTHS

- Film-Coated Tablet 500 mg (3)
- Uncoated Tablet 250 mg (3)

4 CONTRAINDICATIONS

None (4)

5 WARNINGS AND PRECAUTIONS

- Mineralocorticoid excess: Closely monitor patients with cardiovascular disease. Control hypertension and correct hypokalemia before treatment. Monitor blood pressure, serum potassium and symptoms of fluid retention at least monthly. (5.1)
- Adrenocortical insufficiency: Monitor for symptoms and signs of adrenocortical insufficiency. Increased dosage of corticosteroids may be indicated before, during and after stressful situations. (5.2)
- Hepatotoxicity: Can be severe and fatal. Monitor liver function and modify, interrupt, or discontinue ZYTIGA dosing as recommended. (5.3)
- Increased fractures and mortality in combination with radium Ra 223 dichloride: Use of ZYTIGA plus prednisone/prednisolone in combination with radium Ra 223 dichloride is not recommended. (5.4)
- Embryo-Fetal Toxicity: ZYTIGA can cause fetal harm. Advise males with female partners of reproductive potential to use effective contraception. (5.5, 8.1, 8.3)
- Hypoglycemia: Severe hypoglycemia has been reported in patients with pre-existing diabetes who are taking medications containing thiazolidinediones (including pioglitazone) or repaglinide. Monitor blood glucose in patients with diabetes and assess if antidiabetic agent dose modifications are required. (5.6)

6 ADVERSE REACTIONS

The most common adverse reactions (≥10%) are fatigue, arthralgia, hypertension, nausea, edema, hypokalemia, hot flush, diarrhea, vomiting, upper respiratory infection, cough, and headache. (6.1)

The most common laboratory abnormalities (>20%) are anemia, elevated alkaline phosphatase, hypertriglyceridemia, lymphopenia, hypercholesterolemia, hyperglycemia, and hypokalemia. (6.1)

To report SUSPECTED ADVERSE REACTIONS, contact Janssen Biotech, Inc. at 1-800-526-7736 or FDA at 1-800-FDA-1088 or www.fda.gov/medwatch.

7 DRUG INTERACTIONS

- CYP3A4 Inducers: Avoid concomitant strong CYP3A4 inducers during ZYTIGA treatment. If a strong CYP3A4 inducer must be co-administered, increase the ZYTIGA dosing frequency. (2.5, 7.1)
- CYP2D6 Substrates: Avoid co-administration of ZYTIGA with CYP2D6 substrates that have a narrow therapeutic index. If an alternative treatment cannot be used, exercise caution and consider a dose reduction of the concomitant CYP2D6 substrate. (7.2)

8 USE IN SPECIFIC POPULATIONS

- Do not use ZYTIGA in patients with baseline severe hepatic impairment (Child-Pugh Class C). (8.6)

FULL PRESCRIBING INFORMATION

1 INDICATIONS AND USAGE

ZYTIGA is indicated in combination with prednisone for the treatment of patients with

- Metastatic castration-resistant prostate cancer (CRPC)
- Metastatic high-risk castration-sensitive prostate cancer (CSPC)

2 DOSAGE AND ADMINISTRATION

2.1 Recommended Dose for Metastatic CRPC

The recommended dose of ZYTIGA is 1,000 mg (two 500 mg tablets or four 250 mg tablets) orally once daily with prednisone 5 mg orally twice daily.

2.2 Recommended Dose for Metastatic High-risk CSPC

The recommended dose of ZYTIGA is 1,000 mg (two 500 mg tablets or four 250 mg tablets) orally once daily with prednisone 5 mg administered orally once daily.

2.3 Important Administration Instructions

Patients receiving ZYTIGA should also receive a gonadotropin-releasing hormone (GnRH) analog concurrently or should have had bilateral orchiectomy.

ZYTIGA tablets must be taken as a single dose once daily on an empty stomach. Do not eat food 2 hours before and 1 hour after taking ZYTIGA. The tablets must be swallowed whole with water. Do not crush or chew tablets.

2.4 Dose Modification Guidelines in Hepatic Impairment and Hepatotoxicity

Hepatic Impairment

In patients with baseline moderate hepatic impairment (Child-Pugh Class B), reduce the recommended dose of ZYTIGA to 250 mg once daily. In patients with moderate hepatic impairment monitor ALT, AST, and bilirubin prior to the start of treatment, every week for the first month, every two weeks for the following two months of treatment and monthly thereafter. If elevations in ALT and/or AST greater than 5 × upper limit of normal (ULN) or total bilirubin greater than 3 × ULN occur in patients with baseline moderate hepatic impairment, discontinue ZYTIGA and do not re-treat patients with ZYTIGA [see Use in Specific Populations (8.6)and Clinical Pharmacology (12.3)] .

Do not use ZYTIGA in patients with baseline severe hepatic impairment (Child-Pugh Class C).

Hepatotoxicity

For patients who develop hepatotoxicity during treatment with ZYTIGA (ALT and/or AST greater than 5 × ULN or total bilirubin greater than 3 × ULN), interrupt treatment with ZYTIGA [see Warnings and Precautions (5.3)]. Treatment may be restarted at a reduced dose of 750 mg once daily following return of liver function tests to the patient's baseline or to AST and ALT less than or equal to 2.5 × ULN and total bilirubin less than or equal to 1.5 × ULN .For patients who resume treatment, monitor serum transaminases and bilirubin at a minimum of every two weeks for three months and monthly thereafter.

If hepatotoxicity recurs at the dose of 750 mg once daily, re-treatment may be restarted at a reduced dose of 500 mg once daily following return of liver function tests to the patient's baseline or to AST and ALT less than or equal to 2.5 × ULN and total bilirubin less than or equal to 1.5 × ULN .

If hepatotoxicity recurs at the reduced dose of 500 mg once daily, discontinue treatment with ZYTIGA.

Permanently discontinue ZYTIGA for patients who develop a concurrent elevation of ALT greater than 3 × ULN and total bilirubin greater than 2 × ULN in the absence of biliary obstruction or other causes responsible for the concurrent elevation [see Warnings and Precautions (5.3)] .

2.5 Dose Modification Guidelines for Strong CYP3A4 Inducers

Avoid concomitant strong CYP3A4 inducers (e.g., phenytoin, carbamazepine, rifampin, rifabutin, rifapentine, phenobarbital) during ZYTIGA treatment.

If a strong CYP3A4 inducer must be co-administered, increase the ZYTIGA dosing frequency to twice a day only during the co-administration period (e.g., from 1,000 mg once daily to 1,000 mg twice a day). Reduce the dose back to the previous dose and frequency, if the concomitant strong CYP3A4 inducer is discontinued [see Drug Interactions (7.1)and Clinical Pharmacology (12.3)] .

3 DOSAGE FORMS AND STRENGTHS

Tablets (500 mg): purple, oval-shaped, film-coated tablets debossed with "AA" one side and "500" on the other side.

Tablets (250 mg): white to off-white, oval-shaped tablets debossed with "AA250" on one side.

4 CONTRAINDICATIONS

None.

5 WARNINGS AND PRECAUTIONS

5.1 Hypokalemia, Fluid Retention, and Cardiovascular Adverse Reactions due to Mineralocorticoid Excess

ZYTIGA may cause hypertension, hypokalemia, and fluid retention as a consequence of increased mineralocorticoid levels resulting from CYP17 inhibition [see Clinical Pharmacology (12.1)] . Monitor patients for hypertension, hypokalemia, and fluid retention at least once a month. Control hypertension and correct hypokalemia before and during treatment with ZYTIGA.

In the combined data from 4 placebo-controlled trials using prednisone 5 mg twice daily in combination with 1,000 mg abiraterone acetate daily, grades 3–4 hypokalemia were detected in 4% of patients on the ZYTIGA arm and 2% of patients on the placebo arm. Grades 3–4 hypertension were observed in 2% of patients each arm and grades 3–4 fluid retention in 1% of patients each arm.

In LATITUDE (a randomized placebo-controlled, multicenter clinical trial), which used prednisone 5 mg daily in combination with 1,000 mg abiraterone acetate daily, grades 3–4 hypokalemia were detected in 10% of patients on the ZYTIGA arm and 1% of patients on the placebo arm, grades 3–4 hypertension were observed in 20% of patients on the ZYTIGA arm and 10% of patients on the placebo arm. Grades 3–4 fluid retention occurred in 1% of patients each arm [see Adverse Reactions (6)] .

Closely monitor patients whose underlying medical conditions might be compromised by increases in blood pressure, hypokalemia or fluid retention, such as those with heart failure, recent myocardial infarction, cardiovascular disease, or ventricular arrhythmia. In postmarketing experience, QT prolongation and Torsades de Pointes have been observed in patients who develop hypokalemia while taking ZYTIGA.

The safety of ZYTIGA in patients with left ventricular ejection fraction <50% or New York Heart Association (NYHA) Class III or IV heart failure (in COU-AA-301) or NYHA Class II to IV heart failure (in COU-AA-302 and LATITUDE) has not been established because these patients were excluded from these randomized clinical trials [see Clinical Studies (14)] .

5.2 Adrenocortical Insufficiency

Adrenal insufficiency occurred in 0.3% of 2230 patients taking ZYTIGA and in 0.1% of 1763 patients taking placebo in the combined data of the 5 randomized, placebo-controlled clinical studies. Adrenocortical insufficiency was reported in patients receiving ZYTIGA in combination with prednisone, following interruption of daily steroids and/or with concurrent infection or stress.

Monitor patients for symptoms and signs of adrenocortical insufficiency, particularly if patients are withdrawn from prednisone, have prednisone dose reductions, or experience unusual stress. Symptoms and signs of adrenocortical insufficiency may be masked by adverse reactions associated with mineralocorticoid excess seen in patients treated with ZYTIGA. If clinically indicated, perform appropriate tests to confirm the diagnosis of adrenocortical insufficiency. Increased dosage of corticosteroids may be indicated before, during and after stressful situations [see Warnings and Precautions (5.1)].

5.3 Hepatotoxicity

In postmarketing experience, there have been ZYTIGA-associated severe hepatic toxicity, including fulminant hepatitis, acute liver failure and deaths [see Adverse Reactions (6.2)] .

In the combined data of 5 randomized clinical trials, grade 3–4 ALT or AST increases (at least 5 × ULN) were reported in 6% of 2230 patients who received ZYTIGA, typically during the first 3 months after starting treatment. Patients whose baseline ALT or AST were elevated were more likely to experience liver test elevation than those beginning with normal values. Treatment discontinuation due to ALT and AST increases or abnormal hepatic function occurred in 1.1% of 2230 patients taking ZYTIGA. In these clinical trials, no deaths clearly related to ZYTIGA were reported due to hepatotoxicity events.

Measure serum transaminases (ALT and AST) and bilirubin levels prior to starting treatment with ZYTIGA, every two weeks for the first three months of treatment and monthly thereafter. In patients with baseline moderate hepatic impairment receiving a reduced ZYTIGA dose of 250 mg, measure ALT, AST, and bilirubin prior to the start of treatment, every week for the first month, every two weeks for the following two months of treatment and monthly thereafter. Promptly measure serum total bilirubin, AST, and ALT if clinical symptoms or signs suggestive of hepatotoxicity develop. Elevations of AST, ALT, or bilirubin from the patient's baseline should prompt more frequent monitoring. If at any time AST or ALT rise above five times the ULN, or the bilirubin rises above three times the ULN, interrupt ZYTIGA treatment and closely monitor liver function.

Re-treatment with ZYTIGA at a reduced dose level may take place only after return of liver function tests to the patient's baseline or to AST and ALT less than or equal to 2.5 × ULN and total bilirubin less than or equal to 1.5 × ULN [see Dosage and Administration (2.4)] .

Permanently discontinue ZYTIGA for patients who develop a concurrent elevation of ALT greater than 3 × ULN and total bilirubin greater than 2 × ULN in the absence of biliary obstruction or other causes responsible for the concurrent elevation [see Dosage and Administration (2.4)] .

The safety of ZYTIGA re-treatment of patients who develop AST or ALT greater than or equal to 20 × ULN and/or bilirubin greater than or equal to 10 × ULN is unknown.

5.4 Increased Fractures and Mortality in Combination with Radium Ra 223 Dichloride

ZYTIGA plus prednisone/prednisolone is not recommended for use in combination with radium Ra 223 dichloride outside of clinical trials.

The clinical efficacy and safety of concurrent initiation of ZYTIGA plus prednisone/prednisolone and radium Ra 223 dichloride was assessed in a randomized, placebo-controlled multicenter study (ERA-223 trial) in 806 patients with asymptomatic or mildly symptomatic castration-resistant prostate cancer with bone metastases. The study was unblinded early based on an Independent Data Monitoring Committee recommendation.

At the primary analysis, increased incidences of fractures (28.6% vs 11.4%) and deaths (38.5% vs 35.5%) have been observed in patients who received ZYTIGA plus prednisone/prednisolone in combination with radium Ra 223 dichloride compared to patients who received placebo in combination with ZYTIGA plus prednisone/prednisolone.

5.5 Embryo-Fetal Toxicity

The safety and efficacy of ZYTIGA have not been established in females. Based on animal reproductive studies and mechanism of action, ZYTIGA can cause fetal harm and loss of pregnancy when administered to a pregnant female. In animal reproduction studies, oral administration of abiraterone acetate to pregnant rats during organogenesis caused adverse developmental effects at maternal exposures approximately ≥ 0.03 times the human exposure (AUC) at the recommended dose. Advise males with female partners of reproductive potential to use effective contraception during treatment with ZYTIGA and for 3 weeks after the last dose of ZYTIGA [see Use in Specific Populations (8.1, 8.3)] . ZYTIGA should not be handled by females who are or may become pregnant [see How Supplied/Storage and Handling (16)].

5.6 Hypoglycemia

Severe hypoglycemia has been reported when ZYTIGA was administered to patients with pre-existing diabetes receiving medications containing thiazolidinediones (including pioglitazone) or repaglinide [see Drug Interactions (7.2)] . Monitor blood glucose in patients with diabetes during and after discontinuation of treatment with ZYTIGA. Assess if antidiabetic drug dosage needs to be adjusted to minimize the risk of hypoglycemia.

6 ADVERSE REACTIONS

The following are discussed in more detail in other sections of the labeling:

- Hypokalemia, Fluid Retention, and Cardiovascular Adverse Reactions due to Mineralocorticoid Excess [see Warnings and Precautions (5.1)] .
- Adrenocortical Insufficiency [see Warnings and Precautions (5.2)] .
- Hepatotoxicity [see Warnings and Precautions (5.3)] .
- Increased Fractures and Mortality in Combination with Radium Ra 223 Dichloride [see Warnings and Precautions (5.4)].

6.1 Clinical Trial Experience

Because clinical trials are conducted under widely varying conditions, adverse reaction rates observed in the clinical trials of a drug cannot be directly compared to rates in the clinical trials of another drug and may not reflect the rates observed in clinical practice.

Two randomized placebo-controlled, multicenter clinical trials (COU-AA-301 and COU-AA-302) enrolled patients who had metastatic CRPC in which ZYTIGA was administered orally at a dose of 1,000 mg daily in combination with prednisone 5 mg twice daily in the active treatment arms. Placebo plus prednisone 5 mg twice daily was given to patients on the control arm. A third randomized placebo-controlled, multicenter clinical trial (LATITUDE) enrolled patients who had metastatic high-risk CSPC in which ZYTIGA was administered at a dose of 1,000 mg daily in combination with prednisone 5 mg once daily. Placebos were administered to patients in the control arm. Additionally, two other randomized, placebo-controlled trials were conducted in patients with metastatic CRPC. The safety data pooled from 2230 patients in the 5 randomized controlled trials constitute the basis for the data presented in the Warnings and Precautions, Grade 1–4 adverse reactions, and Grade 1–4 laboratory abnormalities. In all trials, a gonadotropin-releasing hormone (GnRH) analog or prior orchiectomy was required in both arms.

In the pooled data, median treatment duration was 11 months (0.1, 43) for ZYTIGA-treated patients and 7.2 months (0.1, 43) for placebo-treated patients. The most common adverse reactions (≥10%) that occurred more commonly (>2%) in the ZYTIGA arm were fatigue, arthralgia, hypertension, nausea, edema, hypokalemia, hot flush, diarrhea, vomiting, upper respiratory infection, cough, and headache. The most common laboratory abnormalities (>20%) that occurred more commonly (≥2%) in the ZYTIGA arm were anemia, elevated alkaline phosphatase, hypertriglyceridemia, lymphopenia, hypercholesterolemia, hyperglycemia, and hypokalemia. Grades 3–4 adverse events were reported for 53% of patients in the ZYTIGA arm and 46% of patients in the placebo arm. Treatment discontinuation was reported in 14% of patients in the ZYTIGA arm and 13% of patients in the placebo arm. The common adverse events (≥1%) resulting in discontinuation of ZYTIGA and prednisone were hepatotoxicity and cardiac disorders.

Deaths associated with treatment-emergent adverse events were reported for 7.5% of patients in the ZYTIGA arm and 6.6% of patients in the placebo arm. Of the patients in the ZYTIGA arm, the most common cause of death was disease progression (3.3%). Other reported causes of death in ≥5 patients included pneumonia, cardio-respiratory arrest, death (no additional information), and general physical health deterioration.

COU-AA-301: Metastatic CRPC Following Chemotherapy

COU-AA-301 enrolled 1195 patients with metastatic CRPC who had received prior docetaxel chemotherapy. Patients were not eligible if AST and/or ALT ≥2.5 × ULN in the absence of liver metastases. Patients with liver metastases were excluded if AST and/or ALT >5 × ULN.

Table 1 shows adverse reactions on the ZYTIGA arm in COU-AA-301 that occurred with a ≥2% absolute increase in frequency compared to placebo or were events of special interest. The median duration of treatment with ZYTIGA with prednisone was 8 months.

Table 1: Adverse Reactions due to ZYTIGA in COU-AA-301
 | ZYTIGA with Prednisone (N=791) |  | Placebo with Prednisone (N=394)
System/Organ Class | All Grades [Adverse events graded according to CTCAE version 3.0.] | Grade 3–4 | All Grades | Grade 3–4
Adverse reaction | % | % | % | %
Musculoskeletal and connective tissue disorders
Joint swelling/discomfort [Includes terms Arthritis, Arthralgia, Joint swelling, and Joint stiffness.] | 30 | 4.2 | 23 | 4.1
Muscle discomfort [Includes terms Muscle spasms, Musculoskeletal pain, Myalgia, Musculoskeletal discomfort, and Musculoskeletal stiffness.] | 26 | 3.0 | 23 | 2.3
General disorders
Edema [Includes terms Edema, Edema peripheral, Pitting edema, and Generalized edema.] | 27 | 1.9 | 18 | 0.8
Vascular disorders
Hot flush | 19 | 0.3 | 17 | 0.3
Hypertension | 8.5 | 1.3 | 6.9 | 0.3
Gastrointestinal disorders
Diarrhea | 18 | 0.6 | 14 | 1.3
Dyspepsia | 6.1 | 0 | 3.3 | 0
Infections and infestations
Urinary tract infection | 12 | 2.1 | 7.1 | 0.5
Upper respiratory tract infection | 5.4 | 0 | 2.5 | 0
Respiratory, thoracic and mediastinal disorders
Cough | 11 | 0 | 7.6 | 0
Renal and urinary disorders
Urinary frequency | 7.2 | 0.3 | 5.1 | 0.3
Nocturia | 6.2 | 0 | 4.1 | 0
Injury, poisoning and procedural complications
Fractures [Includes all fractures with the exception of pathological fracture.] | 5.9 | 1.4 | 2.3 | 0
Cardiac disorders
Arrhythmia [Includes terms Arrhythmia, Tachycardia, Atrial fibrillation, Supraventricular tachycardia, Atrial tachycardia, Ventricular tachycardia, Atrial flutter, Bradycardia, Atrioventricular block complete, Conduction disorder, and Bradyarrhythmia.] | 7.2 | 1.1 | 4.6 | 1.0
Chest pain or chest discomfort [Includes terms Angina pectoris, Chest pain, and Angina unstable. Myocardial infarction or ischemia occurred more commonly in the placebo arm than in the ZYTIGA arm (1.3% vs. 1.1% respectively).] | 3.8 | 0.5 | 2.8 | 0
Cardiac failure [Includes terms Cardiac failure, Cardiac failure congestive, Left ventricular dysfunction, Cardiogenic shock, Cardiomegaly, Cardiomyopathy, and Ejection fraction decreased.] | 2.3 | 1.9 | 1.0 | 0.3

Table 2 shows laboratory abnormalities of interest from COU-AA-301.

Table 2: Laboratory Abnormalities of Interest in COU-AA-301
 | ZYTIGA with Prednisone (N=791) |  | Placebo with Prednisone (N=394)
Laboratory Abnormality | All Grades (%) | Grade 3–4 (%) | All Grades (%) | Grade 3–4 (%)
Hypertriglyceridemia | 63 | 0.4 | 53 | 0
High AST | 31 | 2.1 | 36 | 1.5
Hypokalemia | 28 | 5.3 | 20 | 1.0
Hypophosphatemia | 24 | 7.2 | 16 | 5.8
High ALT | 11 | 1.4 | 10 | 0.8
High Total Bilirubin | 6.6 | 0.1 | 4.6 | 0

COU-AA-302: Metastatic CRPC Prior to Chemotherapy

COU-AA-302 enrolled 1088 patients with metastatic CRPC who had not received prior cytotoxic chemotherapy. Patients were ineligible if AST and/or ALT ≥2.5 × ULN and patients were excluded if they had liver metastases.

Table 3 shows adverse reactions on the ZYTIGA arm in COU-AA-302 that occurred in ≥5% of patients with a ≥2% absolute increase in frequency compared to placebo. The median duration of treatment with ZYTIGA with prednisone was 13.8 months.

Table 3: Adverse Reactions in ≥5% of Patients on the ZYTIGA Arm in COU-AA-302
 | ZYTIGA with Prednisone (N=542) |  | Placebo with Prednisone (N=540)
System/Organ Class | All Grades [Adverse events graded according to CTCAE version 3.0.] | Grade 3–4 | All Grades | Grade 3–4
Adverse reaction | % | % | % | %
General disorders
Fatigue | 39 | 2.2 | 34 | 1.7
Edema [Includes terms Edema peripheral, Pitting edema, and Generalized edema.] | 25 | 0.4 | 21 | 1.1
Pyrexia | 8.7 | 0.6 | 5.9 | 0.2
Musculoskeletal and connective tissue disorders
Joint swelling/discomfort [Includes terms Arthritis, Arthralgia, Joint swelling, and Joint stiffness.] | 30 | 2.0 | 25 | 2.0
Groin pain | 6.6 | 0.4 | 4.1 | 0.7
Gastrointestinal disorders
Constipation | 23 | 0.4 | 19 | 0.6
Diarrhea | 22 | 0.9 | 18 | 0.9
Dyspepsia | 11 | 0.0 | 5.0 | 0.2
Vascular disorders
Hot flush | 22 | 0.2 | 18 | 0.0
Hypertension | 22 | 3.9 | 13 | 3.0
Respiratory, thoracic and mediastinal disorders
Cough | 17 | 0.0 | 14 | 0.2
Dyspnea | 12 | 2.4 | 9.6 | 0.9
Psychiatric disorders
Insomnia | 14 | 0.2 | 11 | 0.0
Injury, poisoning and procedural complications
Contusion | 13 | 0.0 | 9.1 | 0.0
Falls | 5.9 | 0.0 | 3.3 | 0.0
Infections and infestations
Upper respiratory tract infection | 13 | 0.0 | 8.0 | 0.0
Nasopharyngitis | 11 | 0.0 | 8.1 | 0.0
Renal and urinary disorders
Hematuria | 10 | 1.3 | 5.6 | 0.6
Skin and subcutaneous tissue disorders
Rash | 8.1 | 0.0 | 3.7 | 0.0

Table 4 shows laboratory abnormalities that occurred in greater than 15% of patients, and more frequently (>5%) in the ZYTIGA arm compared to placebo in COU-AA-302.

Table 4: Laboratory Abnormalities in >15% of Patients in the ZYTIGA Arm of COU-AA-302
 | ZYTIGA with Prednisone (N=542) |  | Placebo with Prednisone (N=540)
Laboratory Abnormality | Grade 1–4 % | Grade 3–4 % | Grade 1–4 % | Grade 3–4 %
Hematology
Lymphopenia | 38 | 8.7 | 32 | 7.4
Chemistry
Hyperglycemia [Based on non-fasting blood draws] | 57 | 6.5 | 51 | 5.2
High ALT | 42 | 6.1 | 29 | 0.7
High AST | 37 | 3.1 | 29 | 1.1
Hypernatremia | 33 | 0.4 | 25 | 0.2
Hypokalemia | 17 | 2.8 | 10 | 1.7

LATITUDE: Patients with Metastatic High-risk CSPC

LATITUDE enrolled 1199 patients with newly-diagnosed metastatic, high-risk CSPC who had not received prior cytotoxic chemotherapy. Patients were ineligible if AST and/or ALT ≥2.5 × ULN or if they had liver metastases. All the patients received GnRH analogs or had prior bilateral orchiectomy during the trial. The median duration of treatment with ZYTIGA and prednisone was 24 months.

Table 5 shows adverse reactions on the ZYTIGA arm that occurred in ≥5% of patients with a ≥2% absolute increase in frequency compared to those on the placebos arm.

Table 5: Adverse Reactions in ≥5% of Patients on the ZYTIGA Arm in LATITUDE [All patients were receiving an GnRH agonist or had undergone orchiectomy.]
 | ZYTIGA with Prednisone (N=597) |  | Placebos (N=602)
System/Organ Class Adverse reaction | All Grades [Adverse events graded according to CTCAE version 4.0] % | Grade 3–4 % | All Grades % | Grade 3–4 %
Vascular disorders
Hypertension | 37 | 20 | 13 | 10
Hot flush | 15 | 0.0 | 13 | 0.2
Metabolism and nutrition disorders
Hypokalemia | 20 | 10 | 3.7 | 1.3
Investigations
Alanine aminotransferase increased [Reported as an adverse event or reaction] | 16 | 5.5 | 13 | 1.3
Aspartate aminotransferase increased | 15 | 4.4 | 11 | 1.5
Infections and infestations
Urinary tract infection | 7.0 | 1.0 | 3.7 | 0.8
Upper respiratory tract infection | 6.7 | 0.2 | 4.7 | 0.2
Nervous system disorders
Headache | 7.5 | 0.3 | 5.0 | 0.2
Respiratory, Thoracic and Mediastinal Disorders
Cough [Including cough, productive cough, upper airway cough syndrome] | 6.5 | 0.0 | 3.2 | 0

Table 6 shows laboratory abnormalities that occurred in >15% of patients, and more frequently (>5%) in the ZYTIGA arm compared to placebos.

Table 6: Laboratory Abnormalities in >15% of Patients in the ZYTIGA Arm of LATITUDE
 | ZYTIGA with Prednisone (N=597) |  | Placebos (N=602)
Laboratory Abnormality | Grade 1–4 % | Grade 3–4 % | Grade 1–4 % | Grade 3–4 %
Hematology
Lymphopenia | 20 | 4.1 | 14 | 1.8
Chemistry
Hypokalemia | 30 | 9.6 | 6.7 | 1.3
Elevated ALT | 46 | 6.4 | 45 | 1.3
Elevated total bilirubin | 16 | 0.2 | 6.2 | 0.2

Cardiovascular Adverse Reactions

In the combined data of 5 randomized, placebo-controlled clinical studies, cardiac failure occurred more commonly in patients on the ZYTIGA arm compared to patients on the placebo arm (2.6% versus 0.9%). Grade 3–4 cardiac failure occurred in 1.3% of patients taking ZYTIGA and led to 5 treatment discontinuations and 4 deaths. Grade 3–4 cardiac failure occurred in 0.2% of patients taking placebo. There were no treatment discontinuations and two deaths due to cardiac failure in the placebo group.

In the same combined data, the majority of arrhythmias were grade 1 or 2. There was one death associated with arrhythmia and three patients with sudden death in the ZYTIGA arms and five deaths in the placebo arms. There were 7 (0.3%) deaths due to cardiorespiratory arrest in the ZYTIGA arms and 2 (0.1%) deaths in the placebo arms. Myocardial ischemia or myocardial infarction led to death in 3 patients in the placebo arms and 3 deaths in the ZYTIGA arms.

6.2 Postmarketing Experience

The following additional adverse reactions have been identified during post approval use of ZYTIGA with prednisone. Because these reactions are reported voluntarily from a population of uncertain size, it is not always possible to reliably estimate their frequency or establish a causal relationship to drug exposure.

Respiratory, Thoracic and Mediastinal Disorders:non-infectious pneumonitis.

Musculoskeletaland Connective Tissue Disorders:myopathy, including rhabdomyolysis.

Hepatobiliary Disorders:fulminant hepatitis, including acute hepatic failure and death.

Cardiac Disorders:QT prolongation and Torsades de Pointes (observed in patients who developed hypokalemia or had underlying cardiovascular conditions).

Immune System Disorders – Hypersensitivity:anaphylactic reactions (severe allergic reactions that include, but are not limited to difficulty swallowing or breathing, swollen face, lips, tongue or throat, or an itchy rash (urticaria)).

7 DRUG INTERACTIONS

7.1 Drugs that Inhibit or Induce CYP3A4 Enzymes

Based on in vitrodata, ZYTIGA is a substrate of CYP3A4.

In a dedicated drug interaction trial, co-administration of rifampin, a strong CYP3A4 inducer, decreased exposure of abiraterone by 55%. Avoid concomitant strong CYP3A4 inducers during ZYTIGA treatment. If a strong CYP3A4 inducer must be co-administered, increase the ZYTIGA dosing frequency [see Dosage and Administration (2.5)and Clinical Pharmacology (12.3)] .

In a dedicated drug interaction trial, co-administration of ketoconazole, a strong inhibitor of CYP3A4, had no clinically meaningful effect on the pharmacokinetics of abiraterone [see Clinical Pharmacology (12.3)] .

7.2 Effects of Abiraterone on Drug Metabolizing Enzymes

ZYTIGA is an inhibitor of the hepatic drug-metabolizing enzymes CYP2D6 and CYP2C8. In a CYP2D6 drug-drug interaction trial, the Cmaxand AUC of dextromethorphan (CYP2D6 substrate) were increased 2.8- and 2.9-fold, respectively, when dextromethorphan was given with abiraterone acetate 1,000 mg daily and prednisone 5 mg twice daily. Avoid co-administration of abiraterone acetate with substrates of CYP2D6 with a narrow therapeutic index (e.g., thioridazine). If alternative treatments cannot be used, consider a dose reduction of the concomitant CYP2D6 substrate drug [see Clinical Pharmacology (12.3)] .

In a CYP2C8 drug-drug interaction trial in healthy subjects, the AUC of pioglitazone (CYP2C8 substrate) was increased by 46% when pioglitazone was given together with a single dose of 1,000 mg abiraterone acetate. Therefore, patients should be monitored closely for signs of toxicity related to a CYP2C8 substrate with a narrow therapeutic index if used concomitantly with ZYTIGA [see Clinical Pharmacology (12.3)and Warnings and Precautions (5.6)] .

8 USE IN SPECIFIC POPULATIONS

8.1 Pregnancy

Risk Summary

The safety and efficacy of ZYTIGA have not been established in females. Based on findings from animal studies and the mechanism of action, ZYTIGA can cause fetal harm and potential loss of pregnancy.

There are no human data on the use of ZYTIGA in pregnant women. In animal reproduction studies, oral administration of abiraterone acetate to pregnant rats during organogenesis caused adverse developmental effects at maternal exposures approximately ≥ 0.03 times the human exposure (AUC) at the recommended dose (see Data).

Data

Animal Data

In an embryo-fetal developmental toxicity study in rats, abiraterone acetate caused developmental toxicity when administered at oral doses of 10, 30 or 100 mg/kg/day throughout the period of organogenesis (gestational days 6–17). Findings included embryo-fetal lethality (increased post implantation loss and resorptions and decreased number of live fetuses), fetal developmental delay (skeletal effects) and urogenital effects (bilateral ureter dilation) at doses ≥10 mg/kg/day, decreased fetal ano-genital distance at ≥30 mg/kg/day, and decreased fetal body weight at 100 mg/kg/day. Doses ≥10 mg/kg/day caused maternal toxicity. The doses tested in rats resulted in systemic exposures (AUC) approximately 0.03, 0.1 and 0.3 times, respectively, the AUC in patients.

8.2 Lactation

Risk Summary

The safety and efficacy of ZYTIGA have not been established in females. There is no information available on the presence of abiraterone in human milk, or on the effects on the breastfed child or milk production.

8.3 Females and Males of Reproductive Potential

Contraception

Males

Based on findings in animal reproduction studies and its mechanism of action, advise males with female partners of reproductive potential to use effective contraception during treatment and for 3 weeks after the final dose of ZYTIGA [see Use in Specific Populations (8.1)] .

Infertility

Based on animal studies, ZYTIGA may impair reproductive function and fertility in males of reproductive potential [see Nonclinical Toxicology (13.1)].

8.4 Pediatric Use

Safety and effectiveness of ZYTIGA in pediatric patients have not been established.

8.5 Geriatric Use

Of the total number of patients receiving ZYTIGA in randomized clinical trials, 70% of patients were 65 years and over and 27% were 75 years and over. No overall differences in safety or effectiveness were observed between these elderly patients and younger patients. Other reported clinical experience has not identified differences in responses between the elderly and younger patients, but greater sensitivity of some older individuals cannot be ruled out.

8.6 Patients with Hepatic Impairment

The pharmacokinetics of abiraterone were examined in subjects with baseline mild (N=8) or moderate (N=8) hepatic impairment (Child-Pugh Class A and B, respectively) and in 8 healthy control subjects with normal hepatic function. The systemic exposure (AUC) of abiraterone after a single oral 1,000 mg dose of ZYTIGA increased by approximately 1.1-fold and 3.6-fold in subjects with mild and moderate baseline hepatic impairment, respectively compared to subjects with normal hepatic function.

In another trial, the pharmacokinetics of abiraterone were examined in subjects with baseline severe (N=8) hepatic impairment (Child-Pugh Class C) and in 8 healthy control subjects with normal hepatic function. The systemic exposure (AUC) of abiraterone increased by approximately 7-fold and the fraction of free drug increased 2-fold in subjects with severe baseline hepatic impairment compared to subjects with normal hepatic function.

No dosage adjustment is necessary for patients with baseline mild hepatic impairment. In patients with baseline moderate hepatic impairment (Child-Pugh Class B), reduce the recommended dose of ZYTIGA to 250 mg once daily. Do not use ZYTIGA in patients with baseline severe hepatic impairment (Child-Pugh Class C). If elevations in ALT or AST >5 × ULN or total bilirubin >3 × ULN occur in patients with baseline moderate hepatic impairment, discontinue ZYTIGA treatment [see Dosage and Administration (2.4)and Clinical Pharmacology (12.3)] .

For patients who develop hepatotoxicity during treatment, interruption of treatment and dosage adjustment may be required [see Dosage and Administration (2.4), Warnings and Precautions (5.3), and Clinical Pharmacology (12.3)].

8.7 Patients with Renal Impairment

No dosage adjustment is necessary for patients with renal impairment [see Clinical Pharmacology (12.3)] .

10 OVERDOSAGE

Human experience of overdose with ZYTIGA is limited.

There is no specific antidote. In the event of an overdose, stop ZYTIGA, undertake general supportive measures, including monitoring for arrhythmias and cardiac failure and assess liver function.

11 DESCRIPTION

Abiraterone acetate, the active ingredient of ZYTIGA® is the acetyl ester of abiraterone. Abiraterone is an inhibitor of CYP17 (17α-hydroxylase/C17,20-lyase). Each ZYTIGA tablet contains either 250 mg or 500 mg of abiraterone acetate. Abiraterone acetate is designated chemically as (3β)-17-(3-pyridinyl) androsta-5,16-dien-3-yl acetate and its structure is:

Abiraterone acetate is a white to off-white, non-hygroscopic, crystalline powder. Its molecular formula is C26H33NO2 and it has a molecular weight of 391.55. Abiraterone acetate is a lipophilic compound with an octanol-water partition coefficient of 5.12 (Log P) and is practically insoluble in water. The pKa of the aromatic nitrogen is 5.19.

ZYTIGA tablets are available in 500 mg film-coated tablets and 250 mg uncoated tablets with the following inactive ingredients:

- 500 mg film-coated tablets: colloidal silicon dioxide, croscarmellose sodium, hypromellose, lactose monohydrate, magnesium stearate, silicified microcrystalline cellulose, and sodium lauryl sulfate. The coating, Opadry®II Purple, contains iron oxide black, iron oxide red, polyethylene glycol, polyvinyl alcohol, talc, and titanium dioxide.
- 250 mg uncoated tablets: colloidal silicon dioxide, croscarmellose sodium, lactose monohydrate, magnesium stearate, microcrystalline cellulose, povidone, and sodium lauryl sulfate.

12 CLINICAL PHARMACOLOGY

12.1 Mechanism of Action

Abiraterone acetate (ZYTIGA) is converted in vivo to abiraterone, an androgen biosynthesis inhibitor, that inhibits 17 α-hydroxylase/C17,20-lyase (CYP17). This enzyme is expressed in testicular, adrenal, and prostatic tumor tissues and is required for androgen biosynthesis.

CYP17 catalyzes two sequential reactions: 1) the conversion of pregnenolone and progesterone to their 17α-hydroxy derivatives by 17α-hydroxylase activity and 2) the subsequent formation of dehydroepiandrosterone (DHEA) and androstenedione, respectively, by C17, 20 lyase activity. DHEA and androstenedione are androgens and are precursors of testosterone. Inhibition of CYP17 by abiraterone can also result in increased mineralocorticoid production by the adrenals [see Warnings and Precautions (5.1)] .

Androgen sensitive prostatic carcinoma responds to treatment that decreases androgen levels. Androgen deprivation therapies, such as treatment with GnRH agonists or orchiectomy, decrease androgen production in the testes but do not affect androgen production by the adrenals or in the tumor.

ZYTIGA decreased serum testosterone and other androgens in patients in the placebo-controlled clinical trial. It is not necessary to monitor the effect of ZYTIGA on serum testosterone levels.

Changes in serum prostate specific antigen (PSA) levels may be observed but have not been shown to correlate with clinical benefit in individual patients.

12.2 Pharmacodynamics

Cardiac Electrophysiology

In a multi-center, open-label, single-arm trial, 33 patients with metastatic CRPC received ZYTIGA orally at a dose of 1,000 mg once daily at least 1 hour before or 2 hours after a meal in combination with prednisone 5 mg orally twice daily. Assessments up to Cycle 2 Day 2 showed no large changes in the QTc interval (i.e., >20 ms) from baseline. However, small increases in the QTc interval (i.e., <10 ms) due to abiraterone acetate cannot be excluded due to study design limitations.

12.3 Pharmacokinetics

Following administration of abiraterone acetate, the pharmacokinetics of abiraterone have been studied in healthy subjects and in patients with metastatic CRPC. In vivo, abiraterone acetate is converted to abiraterone. In clinical studies, abiraterone acetate plasma concentrations were below detectable levels (<0.2 ng/mL) in >99% of the analyzed samples.

Absorption

Following oral administration of abiraterone acetate to patients with metastatic CRPC, the median time to reach maximum plasma abiraterone concentrations is 2 hours. Abiraterone accumulation is observed at steady-state, with a 2-fold higher exposure (steady-state AUC) compared to a single 1,000 mg dose of abiraterone acetate.

At the dose of 1,000 mg daily in patients with metastatic CRPC, steady-state values (mean ± SD) of Cmax were 226 ± 178 ng/mL and of AUC were 993 ± 639 ng.hr/mL. No major deviation from dose proportionality was observed in the dose range of 250 mg to 1,000 mg. However, the exposure was not significantly increased when the dose was doubled from 1,000 to 2,000 mg (8% increase in the mean AUC).

Effect of Food

Systemic exposure of abiraterone is increased when abiraterone acetate is administered with food. In healthy subjects abiraterone Cmax and AUC0–∞ were approximately 7- and 5-fold higher, respectively, when a single dose of abiraterone acetate was administered with a low-fat meal (7% fat, 300 calories) and approximately 17- and 10-fold higher, respectively, when a single dose of abiraterone acetate was administered with a high-fat (57% fat, 825 calories) meal compared to overnight fasting. Abiraterone AUC0–∞ was approximately 7-fold or 1.6-fold higher, respectively, when a single dose of abiraterone acetate was administered 2 hours after or 1 hour before a medium fat meal (25% fat, 491 calories) compared to overnight fasting.

Systemic exposures of abiraterone in patients with metastatic CRPC, after repeated dosing of abiraterone acetate were similar when abiraterone acetate was taken with low-fat meals for 7 days and increased approximately 2-fold when taken with high-fat meals for 7 days compared to when taken at least 2 hours after a meal and at least 1 hour before a meal for 7 days.

Given the normal variation in the content and composition of meals, taking ZYTIGA with meals has the potential to result in increased and highly variable exposures.

Distribution

Abiraterone is highly bound (>99%) to the human plasma proteins, albumin and alpha-1 acid glycoprotein. The apparent steady-state volume of distribution (mean ± SD) is 19,669 ± 13,358 L.

Elimination

In patients with metastatic CRPC, the mean terminal half-life of abiraterone in plasma (mean ± SD) is 12 ± 5 hours.

Metabolism

Following oral administration of^14C-abiraterone acetate as capsules, abiraterone acetate is hydrolyzed to abiraterone (active metabolite). The conversion is likely through esterase activity (the esterases have not been identified) and is not CYP mediated. The two main circulating metabolites of abiraterone in human plasma are abiraterone sulphate (inactive) and N-oxide abiraterone sulphate (inactive), which account for about 43% of exposure each. CYP3A4 and SULT2A1 are the enzymes involved in the formation of N-oxide abiraterone sulphate and SULT2A1 is involved in the formation of abiraterone sulphate.

Excretion

Following oral administration of^14C-abiraterone acetate, approximately 88% of the radioactive dose is recovered in feces and approximately 5% in urine. The major compounds present in feces are unchanged abiraterone acetate and abiraterone (approximately 55% and 22% of the administered dose, respectively).

Specific Populations

Patients with Hepatic Impairment

The pharmacokinetics of abiraterone was examined in subjects with baseline mild (N=8) or moderate (N=8) hepatic impairment (Child-Pugh Class A and B, respectively) and in 8 healthy control subjects with normal hepatic function. Systemic exposure to abiraterone after a single oral 1,000 mg dose given under fasting conditions increased approximately 1.1-fold and 3.6-fold in subjects with mild and moderate baseline hepatic impairment, respectively. The mean half-life of abiraterone is prolonged to approximately 18 hours in subjects with mild hepatic impairment and to approximately 19 hours in subjects with moderate hepatic impairment.

In another trial, the pharmacokinetics of abiraterone were examined in subjects with baseline severe (N=8) hepatic impairment (Child-Pugh Class C) and in 8 healthy control subjects with normal hepatic function. The systemic exposure (AUC) of abiraterone increased by approximately 7-fold in subjects with severe baseline hepatic impairment compared to subjects with normal hepatic function. In addition, the mean protein binding was found to be lower in the severe hepatic impairment group compared to the normal hepatic function group, which resulted in a two-fold increase in the fraction of free drug in patients with severe hepatic impairment .

Patients with Renal Impairment

The pharmacokinetics of abiraterone were examined in patients with end-stage renal disease (ESRD) on a stable hemodialysis schedule (N=8) and in matched control subjects with normal renal function (N=8). In the ESRD cohort of the trial, a single 1,000 mg ZYTIGA dose was given under fasting conditions 1 hour after dialysis, and samples for pharmacokinetic analysis were collected up to 96 hours post dose. Systemic exposure to abiraterone after a single oral 1,000 mg dose did not increase in subjects with end-stage renal disease on dialysis, compared to subjects with normal renal function .

Drug Interaction Studies

Clinical Studies

Effect of Other Drugs on ZYTIGA

Strong CYP3A4 inducers: In a clinical pharmacokinetic interaction study of healthy subjects pretreated with a strong CYP3A4 inducer (rifampin, 600 mg daily for 6 days) followed by a single dose of abiraterone acetate 1,000 mg, the mean plasma AUC∞ of abiraterone was decreased by 55%.

Strong CYP3A4 inhibitors: Co-administration of ketoconazole, a strong inhibitor of CYP3A4, had no clinically meaningful effect on the pharmacokinetics of abiraterone.

Effect of ZYTIGA on Other Drugs

CYP2D6 substrates: The Cmax and AUC of dextromethorphan (CYP2D6 substrate) were increased 2.8- and 2.9-fold, respectively when dextromethorphan 30 mg was given with abiraterone acetate 1,000 mg daily (plus prednisone 5 mg twice daily). The AUC for dextrorphan, the active metabolite of dextromethorphan, increased approximately 1.3 fold.

CYP1A2 substrates: When abiraterone acetate 1,000 mg daily (plus prednisone 5 mg twice daily) was given with a single dose of 100 mg theophylline (CYP1A2 substrate), no increase in systemic exposure of theophylline was observed.

CYP2C8 substrates: The AUC of pioglitazone (CYP2C8 substrate) was increased by 46% when pioglitazone was given to healthy subjects with a single dose of 1,000 mg abiraterone acetate.

In Vitro Studies

Cytochrome P450 (CYP) Enzymes:Abiraterone is a substrate of CYP3A4 and has the potential to inhibit CYP1A2, CYP2D6, CYP2C8 and to a lesser extent CYP2C9, CYP2C19 and CYP3A4/5.

Transporter Systems: In vitro studies show that at clinically relevant concentrations, abiraterone acetate and abiraterone are not substrates of P-glycoprotein (P-gp) and that abiraterone acetate is an inhibitor of P-gp. In vitro, abiraterone and its major metabolites were shown to inhibit the hepatic uptake transporter OATP1B1. There are no clinical data available to confirm transporter based interaction.

13 NONCLINICAL TOXICOLOGY

13.1 Carcinogenesis, Mutagenesis, and Impairment of Fertility

A two-year carcinogenicity study was conducted in rats at oral abiraterone acetate doses of 5, 15, and 50 mg/kg/day for males and 15, 50, and 150 mg/kg/day for females. Abiraterone acetate increased the combined incidence of interstitial cell adenomas and carcinomas in the testes at all dose levels tested. This finding is considered to be related to the pharmacological activity of abiraterone. Rats are regarded as more sensitive than humans to developing interstitial cell tumors in the testes. Abiraterone acetate was not carcinogenic in female rats at exposure levels up to 0.8 times the human clinical exposure based on AUC. Abiraterone acetate was not carcinogenic in a 6-month study in the transgenic (Tg.rasH2) mouse.

Abiraterone acetate and abiraterone was not mutagenic in an in vitro microbial mutagenesis (Ames) assay or clastogenic in an in vitro cytogenetic assay using primary human lymphocytes or an in vivo rat micronucleus assay.

In repeat-dose toxicity studies in male rats (13- and 26-weeks) and monkeys (39-weeks), atrophy, aspermia/hypospermia, and hyperplasia in the reproductive system were observed at ≥50 mg/kg/day in rats and ≥250 mg/kg/day in monkeys and were consistent with the antiandrogenic pharmacological activity of abiraterone. These effects were observed in rats at systemic exposures similar to humans and in monkeys at exposures approximately 0.6 times the AUC in humans.

In a fertility study in male rats, reduced organ weights of the reproductive system, sperm counts, sperm motility, altered sperm morphology and decreased fertility were observed in animals dosed for 4 weeks at ≥30 mg/kg/day orally. Mating of untreated females with males that received 30 mg/kg/day oral abiraterone acetate resulted in a reduced number of corpora lutea, implantations and live embryos and an increased incidence of pre-implantation loss. Effects on male rats were reversible after 16 weeks from the last abiraterone acetate administration.

In a fertility study in female rats, animals dosed orally for 2 weeks until day 7 of pregnancy at ≥30 mg/kg/day had an increased incidence of irregular or extended estrous cycles and pre-implantation loss (300 mg/kg/day). There were no differences in mating, fertility, and litter parameters in female rats that received abiraterone acetate. Effects on female rats were reversible after 4 weeks from the last abiraterone acetate administration.

The dose of 30 mg/kg/day in rats is approximately 0.3 times the recommended dose of 1,000 mg/day based on body surface area.

In 13- and 26-week studies in rats and 13- and 39-week studies in monkeys, a reduction in circulating testosterone levels occurred with abiraterone acetate at approximately one half the human clinical exposure based on AUC. As a result, decreases in organ weights and toxicities were observed in the male and female reproductive system, adrenal glands, liver, pituitary (rats only), and male mammary glands. The changes in the reproductive organs are consistent with the antiandrogenic pharmacological activity of abiraterone acetate.

13.2 Animal Toxicology and/or Pharmacology

A dose-dependent increase in cataracts was observed in rats after daily oral abiraterone acetate administration for 26 weeks starting at ≥50 mg/kg/day (similar to the human clinical exposure based on AUC). In a 39-week monkey study with daily oral abiraterone acetate administration, no cataracts were observed at higher doses (2 times greater than the clinical exposure based on AUC).

14 CLINICAL STUDIES

The efficacy and safety of ZYTIGA with prednisone was established in three randomized placebo-controlled international clinical studies. All patients in these studies received a GnRH analog or had prior bilateral orchiectomy. Patients with prior ketoconazole treatment for prostate cancer and a history of adrenal gland or pituitary disorders were excluded from these trials. Concurrent use of spironolactone was not allowed during the study period.

COU-AA-301: Patients with metastatic CRPC who had received prior docetaxel chemotherapy

In COU-AA-301 (NCT00638690), a total of 1195 patients were randomized 2:1 to receive either ZYTIGA orally at a dose of 1,000 mg once daily in combination with prednisone 5 mg orally twice daily (N=797) or placebo once daily plus prednisone 5 mg orally twice daily (N=398). Patients randomized to either arm were to continue treatment until disease progression (defined as a 25% increase in PSA over the patient's baseline/nadir together with protocol-defined radiographic progression and symptomatic or clinical progression), initiation of new treatment, unacceptable toxicity or withdrawal.

The following patient demographics and baseline disease characteristics were balanced between the treatment arms. The median age was 69 years (range 39–95) and the racial distribution was 93% Caucasian, 3.6% Black, 1.7% Asian, and 1.6% Other. Eighty-nine percent of patients enrolled had an ECOG performance status score of 0–1 and 45% had a Brief Pain Inventory-Short Form score of ≥4 (patient's reported worst pain over the previous 24 hours). Ninety percent of patients had metastases in bone and 30% had visceral involvement. Seventy percent of patients had radiographic evidence of disease progression and 30% had PSA-only progression. Seventy percent of patients had previously received one cytotoxic chemotherapy regimen and 30% received two regimens.

The protocol pre-specified interim analysis was conducted after 552 deaths and showed a statistically significant improvement in overall survival (OS) in patients treated with ZYTIGA with prednisone compared to patients in the placebo with prednisone arm (Table 7 and Figure 1). An updated survival analysis was conducted when 775 deaths (97% of the planned number of deaths for final analysis) were observed. Results from this analysis were consistent with those from the interim analysis (Table 7).

Table 7: Overall Survival of Patients Treated with Either ZYTIGA or Placebo in Combination with Prednisone in COU-AA-301 (Intent-to-Treat Analysis)
 | ZYTIGA with Prednisone (N=797) | Placebo with Prednisone (N=398)
Primary Survival Analysis
Deaths (%) | 333 (42%) | 219 (55%)
Median survival (months) (95% CI) | 14.8 (14.1, 15.4) | 10.9 (10.2, 12.0)
p-value [p-value is derived from a log-rank test stratified by ECOG performance status score (0–1 vs. 2), pain score (absent vs. present), number of prior chemotherapy regimens (1 vs. 2), and type of disease progression (PSA only vs. radiographic).] | <0.0001
Hazard ratio (95% CI) [Hazard Ratio is derived from a stratified proportional hazards model. Hazard ratio <1 favors ZYTIGA with prednisone.] | 0.646 (0.543, 0.768)
Updated Survival Analysis
Deaths (%) | 501 (63%) | 274 (69%)
Median survival (months) (95% CI) | 15.8 (14.8, 17.0) | 11.2 (10.4, 13.1)
Hazard ratio (95% CI) | 0.740 (0.638, 0.859)

Figure 1: Kaplan-Meier Overall Survival Curves in COU-AA-301 (Intent-to-Treat Analysis)

COU-AA-302: Patients with metastatic CRPC who had not received prior cytotoxic chemotherapy

In COU-AA-302 (NCT00887198), 1088 patients were randomized 1:1 to receive either ZYTIGA orally at a dose of 1,000 mg once daily (N=546) or Placebo orally once daily (N=542). Both arms were given concomitant prednisone 5 mg twice daily. Patients continued treatment until radiographic or clinical (cytotoxic chemotherapy, radiation or surgical treatment for cancer, pain requiring chronic opioids, or ECOG performance status decline to 3 or more) disease progression, unacceptable toxicity or withdrawal. Patients with moderate or severe pain, opiate use for cancer pain, or visceral organ metastases were excluded.

Patient demographics were balanced between the treatment arms. The median age was 70 years. The racial distribution of patients treated with ZYTIGA was 95% Caucasian, 2.8% Black, 0.7% Asian and 1.1% Other. The ECOG performance status was 0 for 76% of patients, and 1 for 24% of patients. Co-primary efficacy endpoints were overall survival and radiographic progression-free survival (rPFS). Baseline pain assessment was 0–1 (asymptomatic) in 66% of patients and 2–3 (mildly symptomatic) in 26% of patients as defined by the Brief Pain Inventory-Short Form (worst pain over the last 24 hours).

Radiographic progression-free survival was assessed with the use of sequential imaging studies and was defined by bone scan identification of 2 or more new bone lesions with confirmation (Prostate Cancer Working Group 2 criteria) and/or modified Response Evaluation Criteria In Solid Tumors (RECIST) criteria for progression of soft tissue lesions. Analysis of rPFS utilized centrally-reviewed radiographic assessment of progression.

The planned final analysis for OS, conducted after 741 deaths (median follow up of 49 months) demonstrated a statistically significant OS improvement in patients treated with ZYTIGA with prednisone compared to those treated with placebo with prednisone (Table 8 and Figure 2). Sixty-five percent of patients on the ZYTIGA arm and 78% of patients on the placebo arm used subsequent therapies that may prolong OS in metastatic CRPC. ZYTIGA was used as a subsequent therapy in 13% of patients on the ZYTIGA arm and 44% of patients on the placebo arm.

Table 8: Overall Survival of Patients Treated with Either ZYTIGA or Placebo in Combination with Prednisone in COU-AA-302 (Intent-to-Treat Analysis)
 | ZYTIGA with Prednisone (N=546) | Placebo with Prednisone (N=542)
Overall Survival
Deaths | 354 (65%) | 387 (71%)
Median survival (months) (95% CI) | 34.7 (32.7, 36.8) | 30.3 (28.7, 33.3)
p-value [p-value is derived from a log-rank test stratified by ECOG performance status score (0 vs. 1).] | 0.0033
Hazard ratio [Hazard Ratio is derived from a stratified proportional hazards model. Hazard ratio <1 favors ZYTIGA with prednisone.] (95% CI) | 0.81 (0.70, 0.93)

Figure 2: Kaplan Meier Overall Survival Curves in COU-AA-302

At the pre-specified rPFS analysis, 150 (28%) patients treated with ZYTIGA with prednisone and 251 (46%) patients treated with placebo with prednisone had radiographic progression. A significant difference in rPFS between treatment groups was observed (Table 9 and Figure 3).

Table 9: Radiographic Progression-free Survival of Patients Treated with Either ZYTIGA or Placebo in Combination with Prednisone in COU-AA-302 (Intent-to-Treat Analysis)
 | ZYTIGA with Prednisone (N=546) | Placebo with Prednisone (N=542)
Radiographic Progression-free Survival
Progression or death | 150 (28%) | 251 (46%)
Median rPFS (months) (95% CI) | NR (11.66, NR) | 8.28 (8.12, 8.54)
p-value [p-value is derived from a log-rank test stratified by ECOG performance status score (0 vs. 1).] | <0.0001
Hazard ratio [Hazard Ratio is derived from a stratified proportional hazards model. Hazard ratio <1 favors ZYTIGA with prednisone.] (95% CI) | 0.425 (0.347, 0.522)
NR=Not reached.

Figure 3: Kaplan Meier Curves of Radiographic Progression-free Survival in COU-AA-302 (Intent-to-Treat Analysis)

The primary efficacy analyses are supported by the following prospectively defined endpoints. The median time to initiation of cytotoxic chemotherapy was 25.2 months for patients in the ZYTIGA arm and 16.8 months for patients in the placebo arm (HR=0.580; 95% CI: [0.487, 0.691], p < 0.0001).

The median time to opiate use for prostate cancer pain was not reached for patients receiving ZYTIGA and was 23.7 months for patients receiving placebo (HR=0.686; 95% CI: [0.566, 0.833], p=0.0001). The time to opiate use result was supported by a delay in patient reported pain progression favoring the ZYTIGA arm.

LATITUDE: Patients with metastatic high-risk CSPC

In LATITUDE (NCT01715285), 1199 patients with metastatic high-risk CSPC were randomized 1:1 to receive either ZYTIGA orally at a dose of 1,000 mg once daily with prednisone 5 mg once daily (N=597) or placebos orally once daily (N=602). High-risk disease was defined as having at least two of three risk factors at baseline: a total Gleason score of ≥8, presence of ≥3 lesions on bone scan, and evidence of measurable visceral metastases. Patients with significant cardiac, adrenal, or hepatic dysfunction were excluded. Patients continued treatment until radiographic or clinical disease progression, unacceptable toxicity, withdrawal or death. Clinical progression was defined as the need for cytotoxic chemotherapy, radiation or surgical treatment for cancer, pain requiring chronic opioids, or ECOG performance status decline to ≥3.

Patient demographics were balanced between the treatment arms. The median age was 67 years among all randomized subjects. The racial distribution of patients treated with ZYTIGA was 69% Caucasian, 2.5% Black, 21% Asian, and 8.1% Other. The ECOG performance status was 0 for 55%, 1 for 42%, and 2 for 3.5% of patients. Baseline pain assessment was 0–1 (asymptomatic) in 50% of patients, 2–3 (mildly symptomatic) in 23% of patients, and ≥4 in 28% of patients as defined by the Brief Pain Inventory-Short Form (worst pain over the last 24 hours).

A major efficacy outcome was overall survival. The pre-specified interim analysis after 406 deaths showed a statistically significant improvement in OS in patients on ZYTIGA with prednisone compared to those on placebos. Twenty-one percent of patients on the ZYTIGA arm and 41% of patients on the placebos arm received subsequent therapies that may prolong OS in metastatic CRPC. An updated survival analysis was conducted when 618 deaths were observed. The median follow-up time was 52 months. Results from this analysis were consistent with those from the pre-specified interim analysis (Table 10 and Figure 4). At the updated analysis, 29% of patients on the ZYTIGA arm and 45% of patients on the placebos arm received subsequent therapies that may prolong OS in metastatic CRPC.

Table 10: Overall Survival of Patients Treated with Either ZYTIGA or Placebos in LATITUDE (Intent-to-Treat Analysis)
 | ZYTIGA with Prednisone (N=597) | Placebos (N=602)
Overall Survival [This is based on the pre-specified interim analysis]
Deaths (%) | 169 (28%) | 237 (39%)
Median survival (months) (95% CI) | NE (NE, NE) | 34.7 (33.1, NE)
p-value [p value is from log-rank test stratified by ECOG PS score (0/1 or 2) and visceral (absent or present).] | <0.0001
Hazard ratio (95% CI) [Hazard Ratio is derived from a stratified proportional hazards model. Hazard ratio <1 favors ZYTIGA with prednisone.] | 0.62 (0.51, 0.76)
Updated Overall Survival
Deaths (%) | 275 (46%) | 343 (57%)
Median survival (months) (95% CI) | 53.3 (48.2, NE) | 36.5 (33.5, 40.0)
Hazard ratio (95% CI) | 0.66 (0.56, 0.78)
NE=Not estimable

Figure 4: Kaplan-Meier Plot of Overall Survival; Intent-to-treat Population in LATITUDE Updated Analysis

The major efficacy outcome was supported by a statistically significant delay in time to initiation of chemotherapy for patients in the ZYTIGA arm compared to those in the placebos arm. The median time to initiation of chemotherapy was not reached for patients on ZYTIGA with prednisone and was 38.9 months for patients on placebos (HR = 0.44; 95% CI: [0.35, 0.56], p < 0.0001).

16 HOW SUPPLIED/STORAGE AND HANDLING

ZYTIGA® (abiraterone acetate) Tablets are available in the strengths and packages listed below:

- ZYTIGA® 500 mg film-coated Tablets
  Purple, oval-shaped tablets debossed with "AA" one side and "500" on the other side.
  NDC 57894-195-06, 60 tablets available in child-resistant high-density polyethylene bottles
- ZYTIGA® 250 mg uncoated Tablets
  White to off-white, oval-shaped tablets debossed with "AA250" on one side.
  NDC 57894-150-12, 120 tablets available in child-resistant high-density polyethylene bottles

Storage and Handling

Store at 20 °C to 25 °C (68 °F to 77 °F); excursions permitted in the range from 15 °C to 30 °C (59 °F to 86 °F) [see USP Controlled Room Temperature].

Keep out of reach of children.

Based on its mechanism of action, ZYTIGA may harm a developing fetus. Women who are pregnant or women who may be pregnant should not handle ZYTIGA 250 mg uncoated tablets or other ZYTIGA tablets if broken, crushed, or damaged without protection, e.g., gloves [see Use in Specific Populations (8.1)] .

17 PATIENT COUNSELING INFORMATION

Advise the patient to read the FDA-approved patient labeling (Patient Information)

Hypokalemia, Fluid Retention, and Cardiovascular Adverse Reactions

- Inform patients that ZYTIGA is associated with hypertension, hypokalemia, and peripheral edema that may lead to QT prolongation and Torsades de Pointes in patients who develop hypokalemia while taking ZYTIGA. Advise patients that their blood pressure, serum potassium and signs and symptoms of fluid retention will be monitored clinically at least monthly. Advise patients to adhere to corticosteroids and to report symptoms of hypertension, hypokalemia, or edema to their healthcare provider [see Warnings and Precautions (5.1)] .

Adrenocortical Insufficiency

- Inform patients that ZYTIGA with prednisone is associated with adrenal insufficiency. Advise patients to report symptoms of adrenocortical insufficiency to their healthcare provider [see Warnings and Precautions (5.2)] .

Hepatotoxicity

- Inform patients that ZYTIGA is associated with severe hepatotoxicity. Inform patients that their liver function will be monitored using blood tests. Advise patients to immediately report symptoms of hepatotoxicity to their healthcare provider [see Warnings and Precautions (5.3)] .

Hypoglycemia

- Inform patients that severe hypoglycemia has been reported when ZYTIGA was administered to patients with pre-existing diabetes who were receiving medications containing thiazolidinediones (including pioglitazone) or repaglinide, antidiabetic drugs. Advise patients with diabetes to monitor glucose levels during and after treatment with ZYTIGA [see Warnings and Precautions (5.6)and Drug Interactions (7.2)].

Use in Combination with Radium Ra 223 Dichloride

- Advise patients that radium Ra 223 dichloride showed an increase in mortality and an increased rate of fracture when used in combination with ZYTIGA plus prednisone/prednisolone. Inform patients to speak with their healthcare provider about any other medications or treatment they are currently taking for prostate cancer [see Warnings and Precautions (5.4)] .

Dosing and Administration

- Inform patients that ZYTIGA is taken once daily with prednisone (once or twice daily according to their healthcare provider's instructions) and to not interrupt or stop either of these medications without consulting their healthcare provider.
- Inform patients receiving GnRH therapy that they need to maintain this treatment during the course of treatment with ZYTIGA.
- Instruct patients to take ZYTIGA tablets as a single dose once daily on an empty stomach. Instruct patients to not eat food 2 hours before and 1 hour after taking ZYTIGA. ZYTIGA taken with food causes increased exposure and may result in adverse reactions. Instruct patients to swallow tablets whole with water and not to crush or chew the tablets [see Dosage and Administration (2.3)] .
- Inform patients that if they miss a dose of ZYTIGA or prednisone, they should take their normal dose the following day. If more than one daily dose is skipped, inform patients to contact their healthcare provider [see Dosage and Administration (2.3)] .

Embryo-Fetal Toxicity

- Inform patients that ZYTIGA may harm a developing fetus and can cause loss of pregnancy.
- Advise males with female partners of reproductive potential to use effective contraception during treatment and for 3 weeks after the final dose of ZYTIGA [see Use in Specific Populations (8.1)] .
- Advise females who are pregnant or women who may be pregnant not to handle ZYTIGA 250 mg uncoated tablets or other ZYTIGA tablets if broken, crushed, or damaged without protection, e.g., gloves [see Use in Specific Populations (8.1)and How Supplied/Storage and Handling (16)] .

Infertility

- Advise male patients that ZYTIGA may impair fertility [see Use in Specific Populations (8.3)] .

Manufactured for:
Janssen Biotech, Inc.
Horsham, PA 19044, USA

For patent information: www.janssenpatents.com

© Johnson & Johnson and its affiliates 2011, 2017, 2024

Revised: 11/2024

PATIENT INFORMATION
ZYTIGA®(Zye- tee- ga)
(abiraterone acetate)
tablets

What is ZYTIGA?
ZYTIGA is a prescription medicine that is used along with prednisone. ZYTIGA is used to treat men with prostate cancer that has spread to other parts of the body.
It is not known if ZYTIGA is safe and effective in females or children.

Before taking ZYTIGA, tell your healthcare provider about all of your medical conditions, including if you:

- have heart problems
- have liver problems
- have diabetes
- have a history of adrenal problems
- have a history of pituitary problems
- are receiving any other treatment for prostate cancer
- are pregnant or plan to become pregnant. ZYTIGA can cause harm to your unborn baby and loss of pregnancy (miscarriage). Females who are or may become pregnant should not handle ZYTIGA uncoated tablets or other ZYTIGA tablets if broken, crushed, or damaged without protection, such as gloves.
- have a partner who is pregnant or may become pregnant.
  - Males who have female partners who are able to become pregnant should use effective birth control (contraception) during treatment with ZYTIGA and for 3 weeks after the last dose of ZYTIGA.
- are breastfeeding or plan to breastfeed. It is not known if ZYTIGA passes into your breastmilk.

Tell your healthcare provider about all the medicines you take or treatments you receive, including prescription and over-the-counter medicines, vitamins, and herbal supplements. ZYTIGA can interact with many other medicines.
You should not start or stop any medicine before you talk with the healthcare provider that prescribed ZYTIGA.
Know the medicines you take. Keep a list of them with you to show to your healthcare provider and pharmacist when you get a new medicine.

How should I take ZYTIGA?

- Take ZYTIGA and prednisone exactly as your healthcare provider tells you.
- Take your prescribed dose of ZYTIGA 1 time a day.
- Your healthcare provider may change your dose if needed.
- Do not change or stop taking your prescribed dose of ZYTIGA or prednisone without talking with your healthcare provider first.
- Take ZYTIGA tablets as a single dose one time a day on an empty stomach. Do not eat food 2 hours before and 1 hour after taking ZYTIGA.
- Do not take ZYTIGA with food.Taking ZYTIGA with food may cause more of the medicine to be absorbed by the body than is needed and this may cause side effects.
- Swallow ZYTIGA tablets whole. Do not crush or chew tablets.
- Take ZYTIGA tablets with water.
- If you miss a dose of ZYTIGA or prednisone, take your prescribed dose the following day. If you miss more than 1 dose, tell your healthcare provider right away.
- Your healthcare provider will do blood tests to check for side effects.

What are the possible side effects of ZYTIGA?
ZYTIGA may cause serious side effects including:

- High blood pressure (hypertension), low blood potassium levels (hypokalemia), fluid retention (edema), and irregular heartbeats can happen during treatment with ZYTIGA. This can be life threatening. To decrease the chance of this happening, you must take prednisone with ZYTIGA exactly as your healthcare provider tells you. Your healthcare provider will check your blood pressure, do blood tests to check your potassium levels, and check for any signs and symptoms of fluid retention every month during treatment with ZYTIGA.
  Tell your healthcare provider if you get any of the following symptoms:

- dizziness
- fast or irregular heartbeats
- feel faint or lightheaded
- headache

- confusion
- muscle weakness
- pain in your legs
- swelling in your legs or feet

- Adrenal problems may happen if you stop taking prednisone, get an infection, or are under stress.
- Severe liver problems. You may develop changes in liver function blood tests. Your healthcare provider will do blood tests to check your liver before treatment with ZYTIGA and during treatment with ZYTIGA. Liver failure may occur, which can lead to death. Tell your healthcare provider right away if you notice any of the following changes:
  - yellowing of the skin or eyes
  - darkening of the urine
  - severe nausea or vomiting
- Increased risk of bone fracture and death when ZYTIGA and prednisone or prednisolone, is used in combination with a type of radiation called radium Ra 223 dichloride. Tell your healthcare provider about any other treatments you are taking for prostate cancer.
- Severe low blood sugar (hypoglycemia). Severe low blood sugar with ZYTIGA can happen in people who have diabetes and take certain antidiabetic medicines. You and your healthcare provider should check your blood sugar levels regularly during treatment with ZYTIGA and after you stop treatment. Your healthcare provider may also need to change the dose of your antidiabetic medicines. Signs and symptoms of low blood sugar may include.

- headache
- drowsiness
- weakness
- dizziness
- confusion

- irritability
- hunger
- fast heartbeat
- sweating
- feeling jittery

The most common side effects of ZYTIGA include:

- feeling very tired
- joint pain
- high blood pressure
- nausea
- swelling in your legs or feet
- low blood potassium levels
- hot flushes
- diarrhea

- vomiting
- infected nose, sinuses, or throat (cold)
- cough
- headache
- low red blood cells (anemia)
- high blood cholesterol and triglycerides
- high blood sugar levels
- certain other abnormal blood tests

ZYTIGA may cause fertility problems in males, which may affect the ability to father children. Talk to your healthcare provider if you have concerns about fertility.
These are not all the possible side effects of ZYTIGA. Call your healthcare provider for medical advice about side effects. You may report side effects to FDA at 1-800-FDA-1088.

How should I store ZYTIGA?

- Store ZYTIGA at room temperature between 68 °F to 77 °F (20 °C to 25 °C).

Keep ZYTIGA and all medicines out of the reach of children.

General information about the safe and effective use of ZYTIGA.
Medicines are sometimes prescribed for purposes other than those listed in a Patient Information leaflet. Do not use ZYTIGA for a condition for which it was not prescribed. Do not give ZYTIGA to other people, even if they have the same symptoms that you have. It may harm them.
You can ask your healthcare provider or pharmacist for information about ZYTIGA that is written for health professionals.

What are the ingredients of ZYTIGA?
Active ingredient: abiraterone acetate
Inactive ingredients:
500 mg film-coated tablets: colloidal silicon dioxide, croscarmellose sodium, hypromellose, lactose monohydrate, magnesium stearate, silicified microcrystalline cellulose, and sodium lauryl sulfate. The film-coating contains iron oxide black, iron oxide red, polyethylene glycol, polyvinyl alcohol, talc, and titanium dioxide.
250 mg uncoated tablets: colloidal silicon dioxide, croscarmellose sodium, lactose monohydrate, magnesium stearate, microcrystalline cellulose, povidone, and sodium lauryl sulfate.
Manufactured for: Janssen Biotech, Inc., Horsham, PA 19044, USA
For more information, call Janssen Biotech, Inc. at 1-800-526-7736 or go to www.Zytiga.com.
For patent information: www.janssenpatents.com
© Johnson & Johnson and its affiliates 2011, 2017, 2024

This Patient Information has been approved by the U.S. Food and Drug Administration.

Revised: 11/2024

PRINCIPAL DISPLAY PANEL - 250 mg Tablet Bottle Label

NDC 57894-150-12
Rx only

Zytiga®
(abiraterone acetate)
tablets

250 mg

Each tablet contains
250 mg of abiraterone acetate.

Warning: Women who are or
may be pregnant should not handle
ZYTIGA without gloves
(see Prescribing Information).

120 tablets

PRINCIPAL DISPLAY PANEL - 500 mg Tablet Bottle Label

NDC 57894-195-06

Zytiga® 500 mg
(abiraterone acetate)
Tablets

Each film-coated tablet contains
500 mg of abiraterone acetate.

Rx only

60 film-coated tablets